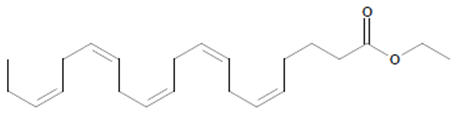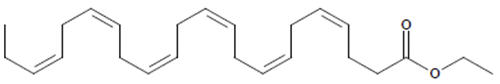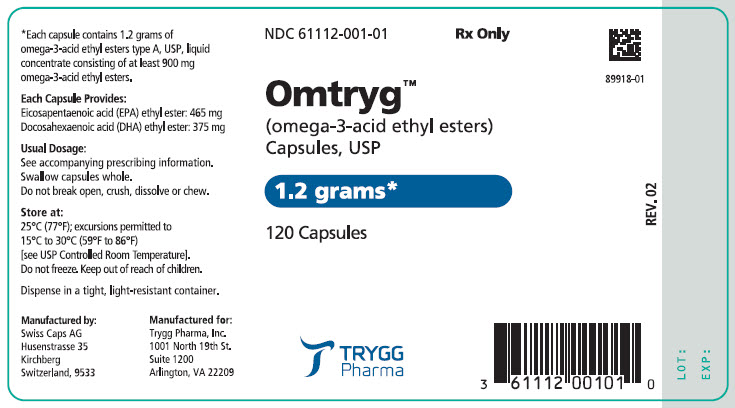 DRUG LABEL: Omtryg
NDC: 61112-001 | Form: CAPSULE
Manufacturer: Trygg Pharma Inc
Category: prescription | Type: HUMAN PRESCRIPTION DRUG LABEL
Date: 20160331

ACTIVE INGREDIENTS: OMEGA-3-ACID ETHYL ESTERS 900 mg/1 1
INACTIVE INGREDIENTS: .ALPHA.-TOCOPHEROL; GELATIN; GLYCERIN; WATER

HIGHLIGHTS OF PRESCRIBING INFORMATION

These highlights do not include all the information needed to use OMTRYG™ safely and effectively. See full prescribing information for OMTRYG.
OMTRYG (omega-3-acid ethyl esters) capsules, USP, for oral use
Initial U.S. Approval: 2004

1 INDICATIONS AND USAGE

OMTRYG is a combination of ethyl esters of omega-3 fatty acids, principally eicosapentaenoic acid (EPA) and docosahexaenoic acid (DHA), indicated as an adjunct to diet to reduce triglyceride (TG) levels in adult patients with severe (≥500 mg/dL) hypertriglyceridemia. (1)

Limitations of Use:
The effect of OMTRYG on the risk for pancreatitis has not been determined. (1)

The effect of OMTRYG on cardiovascular mortality and morbidity has not been determined. (1)

2 DOSAGE AND ADMINISTRATION

- The daily dose of OMTRYG is 4 capsules per day taken as a single dose or as 2 capsules given twice daily. OMTRYG should be taken with meals. (2)
- Patients should be advised to swallow OMTRYG capsules whole. Do not break open, crush, dissolve or chew OMTRYG. (2)

3 DOSAGE FORMS AND STRENGTHS

Capsules: 1.2 grams. (3)

4 CONTRAINDICATIONS

Patients with known hypersensitivity (e.g., anaphylactic reaction) to omega-3-acid ethyl esters or any component of OMTRYG. (4)

5 WARNINGS AND PRECAUTIONS

- In patients with hepatic impairment, monitor ALT and AST levels periodically during therapy. (5.1)
- OMTRYG may increase levels of LDL. Monitor LDL levels periodically during therapy. (5.1)
- Use with caution in patients with known hypersensitivity to fish and/or shellfish. (5.2)
- There is a possible association between omega-3-acid ethyl esters and more frequent recurrences of symptomatic atrial fibrillation or flutter in patients with paroxysmal or persistent atrial fibrillation, particularly within the first months of initiating therapy. (5.3)

6 ADVERSE REACTIONS

The most common adverse reactions (incidence >3% and greater than placebo) were eructation, dyspepsia, and taste perversion. (6)

To report SUSPECTED ADVERSE REACTIONS, contact Trygg Pharma at 1-855-3-OMTRYG (1-855-366-8794) or FDA at 1-800-FDA-1088 or www.fda.gov/medwatch.

7 DRUG INTERACTIONS

Omega-3-acids may prolong bleeding time. Patients taking OMTRYG and an anticoagulant or other drug affecting coagulation (e.g., anti-platelet agents) should be monitored periodically. (7.1)

8 USE IN SPECIFIC POPULATIONS

- Pregnancy: Use during pregnancy only if the potential benefit justifies the potential risk to the fetus. (8.1)

FULL PRESCRIBING INFORMATION

1 INDICATIONS AND USAGE

OMTRYG™ (omega-3-acid ethyl esters) capsules, USP, is indicated as an adjunct to diet to reduce triglyceride (TG) levels in adult patients with severe (≥500 mg/dL) hypertriglyceridemia.

Usage Considerations: Patients should be placed on an appropriate lipid-lowering diet before receiving OMTRYG and should continue this diet during treatment with OMTRYG.

Laboratory studies should be done to ascertain that the lipid levels are consistently abnormal before instituting OMTRYG therapy. Every attempt should be made to control serum lipids with appropriate diet, exercise, weight loss in obese patients, and control of any medical problems, such as diabetes mellitus and hypothyroidism, that are contributing to the lipid abnormalities. Medications known to exacerbate hypertriglyceridemia (such as beta blockers, thiazides, estrogens) should be discontinued or changed if possible prior to consideration of triglyceride-lowering drug therapy.

Limitations of Use:

The effect of OMTRYG on the risk for pancreatitis has not been determined.

The effect of OMTRYG on cardiovascular mortality and morbidity has not been determined.

2 DOSAGE AND ADMINISTRATION

- Assess triglyceride levels carefully before initiating therapy. Identify other causes (e.g., diabetes mellitus, hypothyroidism, or medications) of high triglyceride levels and manage as appropriate. [see Indications and Usage (1)].
- Patients should be placed on an appropriate lipid-lowering diet before receiving OMTRYG and should continue this diet during treatment with OMTRYG.

The daily dose of OMTRYG is 4 capsules per day taken as a single dose (4 capsules) or as 2 capsules given twice daily. OMTRYG should be taken with meals. [see Clinical Pharmacology (12.3)]

Patients should be advised to swallow OMTRYG capsules whole. Do not break open, crush, dissolve or chew OMTRYG.

3 DOSAGE FORMS AND STRENGTHS

OMTRYG (omega-3-acid ethyl esters) capsules, USP, are supplied as 1.2-gram, transparent, soft-gelatin capsules filled with light-yellow oil and bearing the designation TP0001.

4 CONTRAINDICATIONS

OMTRYG is contraindicated in patients with known hypersensitivity (e.g., anaphylactic reaction) to omega-3-acid ethyl esters or any component of OMTRYG.

5 WARNINGS AND PRECAUTIONS

5.1 Monitoring: Laboratory Tests

In patients with hepatic impairment, alanine aminotransferase (ALT) and aspartate aminotransferase (AST) levels should be monitored periodically during therapy with OMTRYG. In some patients, increases in ALT levels without a concurrent increase in AST levels were observed.

In some patients, OMTRYG increases LDL-cholesterol levels. LDL-cholesterol levels should be monitored periodically during therapy with OMTRYG.

5.2 Fish Allergy

OMTRYG contains ethyl esters of omega-3 fatty acids (EPA and DHA) obtained from the oil of several fish sources. It is not known whether patients with allergies to fish and/or shellfish are at increased risk of an allergic reaction to OMTRYG. OMTRYG should be used with caution in patients with known hypersensitivity to fish and/or shellfish.

5.3 Recurrent Atrial Fibrillation (AF) or Flutter

In a double-blind, placebo-controlled trial of 663 patients with symptomatic paroxysmal AF (n=542) or persistent AF (n=121), recurrent AF or flutter was observed in patients randomized to omega-3-acid ethyl esters who received 8 capsules/day for 7 days and 4 capsules/day thereafter for 23 weeks at a higher rate relative to placebo. Patients in this trial had median baseline triglycerides of 127 mg/dL, had no substantial structural heart disease, were taking no anti-arrhythmic therapy (rate control permitted), and were in normal sinus rhythm at baseline.

At 24 weeks, in the paroxysmal AF stratum, there were 129 (47%) first recurrent symptomatic AF or flutter events on placebo and 141 (53%) on omega-3-acid ethyl esters [primary endpoint, HR 1.19; 95% CI 0.93, 1.35]. In the persistent AF stratum, there were 19 (35%) events on placebo and 34 (52%) events on omega-3-acid ethyl esters [HR 1.63; 95% CI 0.91, 2.18]. For both strata combined, the HR was 1.25; 95% CI 1.00, 1.40. Although the clinical significance of these results is uncertain, there is a possible association between omega-3-acid ethyl esters and more frequent recurrences of symptomatic atrial fibrillation or flutter in patients with paroxysmal or persistent atrial fibrillation, particularly within the first 2 to 3 months of initiating therapy.

OMTRYG is not indicated for the treatment of AF or flutter.

6 ADVERSE REACTIONS

6.1 Clinical Trials Experience

Because clinical trials are conducted under widely varying conditions, adverse reaction rates observed in the clinical trials of a drug cannot be directly compared to rates in the clinical trials of another drug and may not reflect the rates observed in practice.

Adverse reactions reported in at least 3% and at a greater rate than placebo for patients treated with omega-3-acid ethyl esters based on pooled data across 23 clinical studies are listed in Table 1.

Table 1. Adverse Reactions Occurring at Incidence ≥3% and Greater than Placebo in Clinical Studies of Omega-3-Acid Ethyl Esters
Body System | Omega-3-Acid Ethyl Esters† (N = 655) |  | Placebo (N = 370)
Adverse Reaction* | n | % | n | %
Eructation | 29 | 4 | 5 | 1
Dyspepsia | 22 | 3 | 6 | 2
Taste perversion | 27 | 4 | 1 | <1
* Studies included subjects with HTG and severe HTG.
† OMTRYG and omega-3-acid ethyl esters each contain, among other components, at least 900 mg per capsule of ethyl esters from omega-3 fatty acids sourced from fish oils.

Additional adverse reactions from clinical studies are listed below:

Digestive System: Constipation, gastrointestinal disorder and vomiting.

Metabolic and Nutritional Disorders: Increased ALT and increased AST.

Skin: Pruritus and rash.

6.2 Postmarketing Experience

The following adverse reactions have been identified during post-approval use of omega-3-acid ethyl esters. Because these reactions are reported voluntarily from a population of uncertain size, it is not always possible to reliably estimate their frequency or establish a causal relationship to drug exposure.

The following events have been reported: anaphylactic reaction, hemorrhagic diathesis.

7 DRUG INTERACTIONS

7.1 Anticoagulants or Other Drugs Affecting Coagulation

Some studies with omega-3-acids demonstrated prolongation of bleeding time. The prolongation of bleeding time reported in these studies has not exceeded normal limits and did not produce clinically significant bleeding episodes. Clinical studies have not been done to thoroughly examine the effect of OMTRYG and concomitant anticoagulants. Patients receiving treatment with OMTRYG and an anticoagulant or other drug affecting coagulation (e.g., anti-platelet agents) should be monitored periodically.

8 USE IN SPECIFIC POPULATIONS

8.1 Pregnancy

Pregnancy Category C: There are no adequate and well-controlled studies in pregnant women. It is unknown whether OMTRYG can cause fetal harm when administered to a pregnant woman or can affect reproductive capacity. OMTRYG should be used during pregnancy only if the potential benefit to the patient justifies the potential risk to the fetus.

Animal Data: Omega-3-acid ethyl esters have been shown to have an embryocidal effect in pregnant rats when given in doses resulting in exposures 7 times the recommended human dose of 4 capsules/day based on a body surface area comparison.

In female rats given oral gavage doses of 100, 600, and 2,000 mg/kg/day beginning 2 weeks prior to mating and continuing through gestation and lactation, no adverse effects were observed in the high dose group (5 times human systemic exposure following an oral dose of 4 capsules/day based on body surface area comparison).

In pregnant rats given oral gavage doses of 1,000, 3,000, and 6,000 mg/kg/day from gestation day 6 through 15, no adverse effects were observed (14 times human systemic exposure following an oral dose of 4 capsules/day based on a body surface area comparison).

In pregnant rats given oral gavage doses of 100, 600, and 2,000 mg/kg/day from gestation day 14 through lactation day 21, no adverse effects were seen at 2,000 mg/kg/day (5 times the human systemic exposure following an oral dose of 4 capsules/day based on a body surface area comparison). However, decreased live births (20% reduction) and decreased survival to postnatal day 4 (40% reduction) were observed in a dose-ranging study using higher doses of 3,000 mg/kg/day (7 times human systemic exposure following an oral dose of 4 capsules/day based on a body surface area comparison).

In pregnant rabbits given oral gavage doses of 375, 750, and 1,500 mg/kg/day from gestation day 7 through 19, no findings were observed in the fetuses in groups given 375 mg/kg/day (2 times human systemic exposure following an oral dose of 4 capsules/day based on a body surface area comparison). However, at higher doses, evidence of maternal toxicity was observed (4 times human systemic exposure following an oral dose of 4 capsules /day based on a body surface area comparison).

8.3 Nursing Mothers

Studies with omega-3-acid ethyl esters have demonstrated excretion in human milk. The effect of this excretion on the infant of a nursing mother is unknown; caution should be exercised when OMTRYG is administered to a nursing mother. An animal study in lactating rats given oral gavage ^14 C-ethyl EPA demonstrated that drug levels were 6 to 14 times higher in milk than in plasma.

8.4 Pediatric Use

Safety and effectiveness in pediatric patients have not been established.

8.5 Geriatric Use

A limited number of patients older than 65 years were enrolled in the clinical studies of omega‑3‑acid ethyl esters. Safety and efficacy findings in subjects older than 60 years did not appear to differ from those of subjects younger than 60 years.

9 DRUG ABUSE AND DEPENDENCE

OMTRYG does not have any known drug abuse or withdrawal effects.

11 DESCRIPTION

OMTRYG, a lipid-regulating agent, is supplied as a liquid-filled gel capsule for oral administration. Each OMTRYG capsule contains 1.2 grams of omega-3-acid ethyl esters type A, USP, liquid concentrate consisting of at least 900 mg omega-3-acid ethyl esters sourced from fish oils. These are predominantly a combination of ethyl esters of eicosapentaenoic acid (EPA - approximately 465 mg) and docosahexaenoic acid (DHA - approximately 375 mg).

The empirical formula of EPA ethyl ester is C22H34O2, and the molecular weight of EPA ethyl ester is 330.51. The structural formula of EPA ethyl ester is:

The empirical formula of DHA ethyl ester is C24H36O2, and the molecular weight of DHA ethyl ester is 356.55. The structural formula of DHA ethyl ester is:

OMTRYG capsules also contain the following inactive ingredients: 4.6 mg α-tocopherol (in a carrier of sunflower oil), gelatin, glycerol, and purified water (components of the capsule shell).

12 CLINICAL PHARMACOLOGY

12.1 Mechanism of Action

The mechanism of action of OMTRYG is not completely understood. Potential mechanisms of action include inhibition of acyl-CoA:1,2-diacylglycerol acyltransferase, increased mitochondrial and peroxisomal ß-oxidation in the liver, decreased lipogenesis in the liver, and increased plasma lipoprotein lipase activity. Omega-3-acid ethyl esters may reduce the synthesis of triglycerides in the liver because EPA and DHA are poor substrates for the enzymes responsible for TG synthesis, and EPA and DHA inhibit esterification of other fatty acids.

12.3 Pharmacokinetics

Systemic Bioavailability: When OMTRYG was administered under fasted condition, on average the peak (Cmax) and total (AUC0-72h) exposure were lower by up to 20 to 80-fold, respectively, for total plasma EPA, and lower by up to 2 to 4-fold, respectively, for total plasma DHA, in comparison to those observed under fed condition (high-fat high-calorie meal). Therefore, OMTRYG should be taken with food.

In healthy volunteers and in patients with hypertriglyceridemia, EPA and DHA were absorbed when administered as ethyl esters orally. Omega-3-acids administered as ethyl esters induced significant, dose-dependent increases in serum phospholipid EPA content, though increases in DHA content were less marked and not dose-dependent when administered as ethyl esters.

Specific Populations:

Age: Uptake of EPA and DHA into serum phospholipids in subjects treated with omega-3-acid ethyl esters was independent of age (<49 years versus ≥49 years).

Gender: Females tended to have more uptake of EPA into serum phospholipids than males. The clinical significance of this is unknown.

Pediatric: Pharmacokinetics of OMTRYG have not been studied.

Renal or Hepatic Impairment: OMTRYG has not been studied in patients with renal or hepatic impairment.

Drug-Drug Interactions: Simvastatin: In a 14-day study of 24 healthy adult subjects, daily co-administration of simvastatin 80 mg with 4 capsules of omega-3-acid ethyl esters did not affect the extent (AUC) or rate (Cmax) of exposure to simvastatin or the major active metabolite, beta-hydroxy simvastatin, at steady state.

Atorvastatin: In a 14-day study of 50 healthy adult subjects, daily co‑administration of atorvastatin 80 mg with 4 capsules of omega-3-acid ethyl esters did not affect AUC or Cmax of exposure to atorvastatin, 2‑hydroxyatorvastatin, or 4-hydroxyatorvastatin at steady state.

Rosuvastatin: In a 14-day study of 48 healthy adult subjects, daily co‑administration of rosuvastatin 40 mg with 4 capsules of omega-3-acid ethyl esters did not affect AUC or Cmax of exposure to rosuvastatin at steady state.

In vitro studies using human liver microsomes indicated that clinically significant cytochrome P450 mediated inhibition by EPA/DHA combinations are not expected in humans.

13 NONCLINICAL TOXICOLOGY

13.1 Carcinogenesis, Mutagenesis, Impairment of Fertility

In a rat carcinogenicity study with oral gavage doses of 100, 600, and 2,000 mg/kg/day, males were treated with omega-3-acid ethyl esters for 101 weeks and females for 89 weeks without an increased incidence of tumors (up to 5 times human systemic exposures following an oral dose of 4 capsules/day based on a body surface area comparison). Standard lifetime carcinogenicity bioassays were not conducted in mice.

Omega-3-acid ethyl esters were not mutagenic or clastogenic with or without metabolic activation in the bacterial mutagenesis (Ames) test with Salmonella typhimurium and Escherichia coli or in the chromosomal aberration assay in Chinese hamster V79 lung cells or human lymphocytes. Omega-3-acid ethyl esters were negative in the in vivo mouse micronucleus assay.

In a rat fertility study with oral gavage doses of 100, 600, and 2,000 mg/kg/day, males were treated for 10 weeks prior to mating and females were treated for 2 weeks prior to and throughout mating, gestation, and lactation. No adverse effect on fertility was observed at 2,000 mg/kg/day (5 times human systemic exposure following an oral dose of 4 capsules/day based on a body surface area comparison).

14 CLINICAL STUDIES

14.1 Severe Hypertriglyceridemia

A randomized, double-blind, placebo-controlled study was conducted to evaluate the efficacy of OMTRYG compared with both placebo and an omega-3-acid ethyl esters product in 254 patients with severe hypertriglyceridemia (500-1500 mg/dL). Patients entered a 6-week wash-out/dietary lead-in period and then were randomized to 12-week treatment with either OMTRYG, omega-3-acid ethyl esters, or placebo (vegetable oil), each administered as 4 capsules once daily. Each capsule of both OMTRYG and omega-3-acid ethyl esters contains, among other components, at least 900 mg of ethyl esters from omega-3 fatty acids sourced from fish oils. The primary endpoint was percent change in serum triglycerides (TG) from baseline to Week 12. The secondary endpoints were percent change in non‑HDL‑C, VLDL‑C, LDL‑C, and HDL‑C from baseline to Week 12. Overall, the mean age was 51 years, 72% were men, 92% were Caucasian, the mean BMI was 33 kg/m^2, and 21% were taking a statin. The baseline median TG level was 675 mg/dL, mean LDL‑C was 87 mg/dL, and mean HDL‑C was 30 mg/dL.

OMTRYG statistically significantly reduced TG at Week 12 compared with placebo (p-value <0.05). The changes in the major lipid parameters for the groups receiving OMTRYG, omega-3-acid ethyl esters, and placebo are shown in Table 2.

Table 2. Median Baseline and Percent Change From Baseline in Lipid Parameters in Patients with Severe Hypertriglyceridemia (≥500 mg/dL)
 | OMTRYG N = 104 |  | Omega-3-Acid Ethyl Esters N=103 |  | Placebo N = 43 |  | Median difference from Placebo
Parameter | BL | % Change | BL | % Change | BL | % Change | OMTRYG vs. Placebo | Omega-3-Acid EE vs. Placebo
TG | 702 | -24.7 | 655 | -26.8 | 624 | -17.4 | -12.2* | -14.0*
Non-HDL-C | 237 | -9.2 | 210 | -3.6 | 222 | -0.8 | -8.5 | -3.5
TC | 270 | -8.1 | 244 | -1.0 | 250 | -0.8 | -6.9 | -1.9
VLDL-C | 153 | -21.2 | 117 | -18.0 | 114 | +5.6 | -28.7** | -23.7*
HDL-C | 28 | 0.0 | 30 | 0.0 | 30 | 0.0 | +3.9 | +5.2
LDL-C | 78 | +20.3 | 85 | +12.8 | 94 | -5.9 | +24.7** | +18.9*
BL = Baseline (mg/dL) median; % Change = Median Percent Change from Baseline; Median difference from placebo = Hodges Lehmann median of all pairwise differences from placebo
* p<0.05, ** p<0.01, statistically significant difference between treatment groups based on the pre-specified Hommel method for controlling Type 1 error among the secondary endpoints.

The effects of omega-3-acid ethyl esters 4 capsules per day were assessed in 2 randomized, placebo-controlled, double-blind, parallel-group studies of 84 adult patients (42 on omega-3-acid ethyl esters, 42 on placebo) with severe hypertriglyceridemia. Patients whose baseline TG levels were between 500 and 2,000 mg/dL were enrolled in these 2 studies of 6 and 16 weeks duration. The median triglyceride and LDL-C levels in these patients were 792 mg/dL and 100 mg/dL, respectively. Median HDL-C level was 23.0 mg/dL.

The changes in the major lipoprotein lipid parameters for the groups receiving omega-3-acid ethyl esters or placebo are shown in Table 3.

Table 3. Median Baseline and Percent Change From Baseline in Lipid Parameters in Patients with Severe Hypertriglyceridemia (≥500 mg/dL)
Parameter | Omega-3-Acid Ethyl Esters* N = 42 |  | Placebo N = 42 |  | Difference
Parameter | BL | % Change | BL | % Change | Difference
TG | 816 | -44.9 | 788 | +6.7 | -51.6
Non-HDL-C | 271 | -13.8 | 292 | -3.6 | -10.2
TC | 296 | -9.7 | 314 | -1.7 | -8.0
VLDL-C | 175 | -41.7 | 175 | -0.9 | -40.8
HDL-C | 22 | +9.1 | 24 | 0.0 | +9.1
LDL-C | 89 | +44.5 | 108 | -4.8 | +49.3
BL = Baseline (mg/dL); % Change = Median Percent Change from Baseline; Difference = Omega-3-acid ethyl esters Median % Change – Placebo Median % Change
* OMTRYG and omega-3-acid ethyl esters each contain, among other components, at least 900 mg per capsule of ethyl esters from omega-3 fatty acids sourced from fish oils.

Omega-3-acid ethyl esters reduced median TG, VLDL-C, and non-HDL-C levels and increased HDL-C from baseline relative to placebo. Treatment with omega-3-acid ethyl esters to reduce very high TG levels may result in elevations in LDL-C and non-HDL-C in some individuals. Patients should be monitored to ensure that the LDL-C level does not increase excessively.

The effect of OMTRYG on the risk of pancreatitis has not been evaluated.

The effect of OMTRYG on cardiovascular mortality and morbidity has not been determined.

16 HOW SUPPLIED/STORAGE AND HANDLING

OMTRYG (omega-3-acid ethyl esters) capsules, USP, 1.2 grams, are supplied as type A transparent soft-gelatin capsules filled with light-yellow oil and bearing the designation TP0001.

Bottles of 120: NDC 61112-001-01

Store at 25°C (77°F); excursions permitted to 15° to 30°C (59° to 86°F) [see USP Controlled Room Temperature]. Do not freeze.

Dispense in a tight, light-resistant container.

17 PATIENT COUNSELING INFORMATION

See FDA-approved Patient Labeling (Patient Information)

- Use OMTRYG with caution in patients with known sensitivity or allergy to fish and/or shellfish [see Warnings and Precautions (5.2)].
- Advise patients that use of lipid-regulating agents does not reduce the importance of adhering to diet [see Dosage and Administration (2)].
- Advise patients to take OMTRYG as prescribed. If a dose is missed, patients should take it as soon as they remember. However, if they miss one day of OMTRYG, they should not double the dose when they take it.
- Advise patients to take OMTRYG capsules with meals [see Dosage and Administration (2)].
- Advise patients to swallow OMTRYG capsules whole. Do not break, open, crush, dissolve or chew OMTRYG [see Dosage and Administration (2)].

Patient labeling is provided as a tear-off leaflet at the end of this full prescribing information.

Manufactured for:

Trygg Pharma, Inc.
1001 North 19th St.
Suite 1200
Arlington, VA 22209

OMTRYG is a registered trademark of Trygg Pharma Inc.

PHARMACIST-DETACH HERE AND GIVE INSTRUCTIONS TO PATIENT

PATIENT INFORMATION

OMTRYG™ (om’ trig)
(Omega-3-Acid Ethyl Esters)
Capsules, USP

Read this Patient Information before you start taking OMTRYG, and each time you get a refill. There may be new information. This information does not take the place of talking with your doctor about your medical condition or your treatment.

What is OMTRYG?

OMTRYG is a prescription medicine used along with a low fat and low cholesterol diet to lower very high triglyceride (fat) levels in adults.

It is not known if OMTRYG changes your risk of having inflammation of your pancreas (pancreatitis).

It is not known if OMTRYG prevents you from having a heart attack or stroke.

It is not known if OMTRYG is safe and effective in children.

Who should not take OMTRYG?

Do not take OMTRYG if you are allergic to omega-3-acid ethyl esters or any of the ingredients in OMTRYG. See the end of this leaflet for a complete list of ingredients in OMTRYG.

What should I tell my doctor before taking OMTRYG?

Before you take OMTRYG, tell your doctor if you:

- have diabetes
- have a low thyroid problem (hypothyroidism)
- have a liver problem
- have a pancreas problem
- have a certain heart rhythm problem called atrial fibrillation or flutter
- are allergic to fish or shellfish. It is not known if people who are allergic to fish or shellfish are also allergic to OMTRYG.
- are pregnant or plan to become pregnant. It is not known if OMTRYG will harm your unborn baby.
- are breastfeeding or plan to breastfeed. OMTRYG can pass into your breast milk. You and your doctor should decide if you will take OMTRYG or breastfeed.

Tell your doctor about all the medicines you take, including prescription and over-the-counter medicine, vitamins, and herbal supplements.

OMTRYG can interact with certain other medicines that you are taking. Using OMTRYG with medicines that affect blood clotting (anticoagulants or blood thinners) may cause serious side effects.

Know the medicines you take. Keep a list of them to show your doctor and pharmacist when you get a new medicine.

How should I take OMTRYG?

- Take OMTRYG exactly as your doctor tells you to take it.
- You should not take more than 4 capsules of OMTRYG each day. Either take all 4 capsules at one time, or 2 capsules two times a day.
- Do not change your dose or stop OMTRYG without talking to your doctor.
- Take OMTRYG with meals.
- Take OMTRYG capsules whole. Do not break, crush, dissolve, or chew OMTRYG capsules before swallowing. If you cannot swallow OMTRYG capsules whole, tell your doctor. You may need a different medicine.
- Your doctor may start you on a diet that is low in saturated fat, cholesterol, carbohydrates, and low in added sugars before giving you OMTRYG. Stay on this diet while you take OMTRYG.
- Your doctor should do blood tests to check your triglyceride, bad cholesterol and liver function levels while you take OMTRYG.

What are the possible side effects of OMTRYG?

OMTRYG may cause serious side effects, including:

- increases in the results of blood tests used to check your liver function (ALT and AST) and your bad cholesterol levels (LDL-C).
- increases in the frequency of a heart rhythm problem (atrial fibrillation or flutter) may especially happen in the first few months of taking OMTRYG if you already have that problem.

The most common side effects of OMTRYG include:

- burping
- upset stomach
- a change in your sense of taste

Talk to your doctor if you have a side effect that bothers you or does not go away.

These are not all the possible side effects of OMTRYG. For more information, ask your doctor or pharmacist.

Call your doctor for medical advice about side effects. You may report side effects to FDA at 1 800-FDA-1088.

How should I store OMTRYG?

- Store OMTRYG at room temperature between 68°F to 77°F (20°C to 25°C).
- Do not freeze OMTRYG.
- Safely throw away medicine that is out of date or no longer needed.

Keep OMTRYG and all medicines out of the reach of children.

General information about the safe and effective use of OMTRYG

Medicines are sometimes prescribed for purposes other than those listed in a Patient Information leaflet. Do not use OMTRYG for a condition for which it was not prescribed. Do not give OMTRYG to other people, even if they have the same symptoms you have. It may harm them.

This Patient Information Leaflet summarizes the most important information about OMTRYG. If you would like more information, talk with your doctor. You can ask your doctor or pharmacist for information about OMTRYG that is written for health professionals.

For more information go to http://www.OMTRYG.com or call 1‑855‑3‑OMTRYG (1‑855‑366‑8794).

What are the ingredients in OMTRYG?

Active Ingredient: omega-3-acid ethyl esters, mostly EPA and DHA

Inactive Ingredients: alpha-tocopherol (in sunflower oil), gelatin, glycerol, purified water

This patient labeling has been approved by the U.S. Food and Drug Administration.

Manufactured for:

Trygg Pharma, Inc.
1001 North 19th St.
Suite 1200
Arlington, VA 22209

PRINCIPAL DISPLAY PANEL

Bottle Label

NDC 61112-001-01 Rx Only

Omtryg™
(omega-3-acid ethyl esters)
Capsules, USP

1.2 grams*

120 Capsules

TRYGG
Pharma

*Each capsule contains 1.2 grams of
omega-3-acid ethyl esters type A, USP, liquid
concentrate consisting of at least 900 mg
omega-3-acid ethyl esters.

Each Capsule Provides:
Eicosapentaenoic acid (EPA) ethyl ester: 465 mg
Docosahexaenoic acid (DHA) ethyl ester: 375 mg

Usual Dosage:
See accompanying prescribing information.
Swallow capsules whole.
Do not break open, crush, dissolve or chew.

Store at:
25°C (77°F); excursions permitted to
15°C to 30°C (59°F to 86°F)
[see USP Controlled Room Temperature].
Do not freeze. Keep out of reach of children.

Dispense in a tight, light-resistant container.

Manufactured by:
Swiss Caps AG
Husenstrasse 35
Kirchberg
Switzerland, 9533

Manufactured for:
Trygg Pharma, Inc.
1001 North 19th St.
Suite 1200
Arlington, VA 22209

89918-01
REV.02
LOT:
EXP: